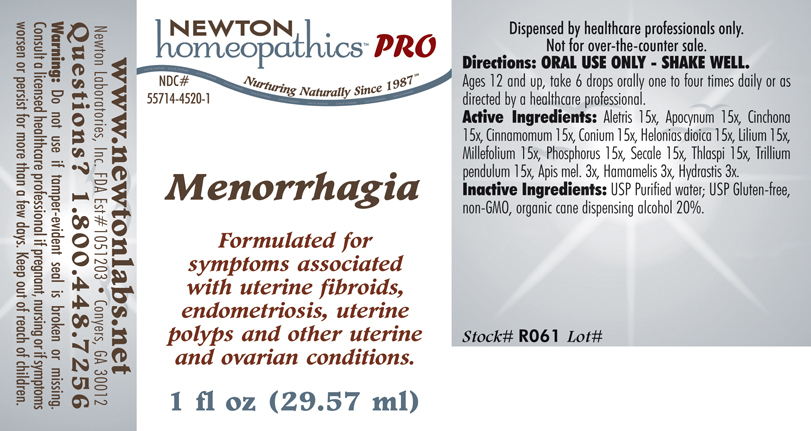 DRUG LABEL: Menorrhagia 
NDC: 55714-4520 | Form: LIQUID
Manufacturer: Newton Laboratories, Inc.
Category: homeopathic | Type: HUMAN PRESCRIPTION DRUG LABEL
Date: 20110601

ACTIVE INGREDIENTS: Aletris Farinosa Root 15 [hp_X]/1 mL; Apocynum Cannabinum Root 15 [hp_X]/1 mL; Cinchona Officinalis Bark 15 [hp_X]/1 mL; Cinnamon 15 [hp_X]/1 mL; Conium Maculatum Flowering Top 15 [hp_X]/1 mL; Chamaelirium Luteum Root 15 [hp_X]/1 mL; Lilium Lancifolium Whole Flowering 15 [hp_X]/1 mL; Achillea Millefolium 15 [hp_X]/1 mL; Phosphorus 15 [hp_X]/1 mL; Claviceps Purpurea Sclerotium 15 [hp_X]/1 mL; Capsella Bursa-pastoris 15 [hp_X]/1 mL; Trillium Erectum Root 15 [hp_X]/1 mL; Apis Mellifera 3 [hp_X]/1 mL; Hamamelis Virginiana Root Bark/stem Bark 3 [hp_X]/1 mL; Goldenseal 3 [hp_X]/1 mL
INACTIVE INGREDIENTS: Alcohol

Menorrhagia

INDICATIONS & USAGE SECTION

Menorrhagia Formulated for associated symptoms such as uterine fibroids, uterine polyps, endometriosis and other uterine and ovarian conditions.

DOSAGE & ADMINISTRATION SECTION

Directions: ORAL USE ONLY - SHAKE WELL. Ages 12 and up, take 6 drops orally one to four times daily or as directed by a healthcare professional.

ACTIVE INGREDIENT SECTION

Aletris 15x, Apocynum 15x, Cinchona 15x, Cinnamomum 15x, Conium 15x, Helonias dioica 15x, Lilium 15x, Millefolium 15x, Phosphorus 15x, Secale 15x, Thlaspi 15x, Trillium pendulum 15x, Apis mel. 3x, Hamamelis 3x, Hydrastis 3x.

PURPOSE SECTION

Formulated for associated symptoms such as uterine fibroids, uterine polyps, endometriosis and other uterine and ovarian conditions.

INACTIVE INGREDIENT SECTION

Inactive Ingredients: USP Purified Water; USP Gluten-free, non-GMO, organic cane dispensing alcohol 20%.

QUESTIONS SECTION

www.newtonlabs.net Newton Laboratories, Inc. FDA Est # 1051203 - Conyers, GA 30012
Questions? 1.800.448.7256

WARNINGS SECTION

Warning: Do not use if tamper - evident seal is broken or missing. Consult a licensed healthcare professional if pregnant, nursing or if symptoms worsen or persist for more than a few days. Keep out of reach of children.

PREGNANCY OR BREAST FEEDING SECTION

Consult a licensed healthcare professional if pregnant, nursing or if symptoms worsen or persist for more than a few days.

KEEP OUT OF REACH OF CHILDREN SECTION

Keep out of reach of children.